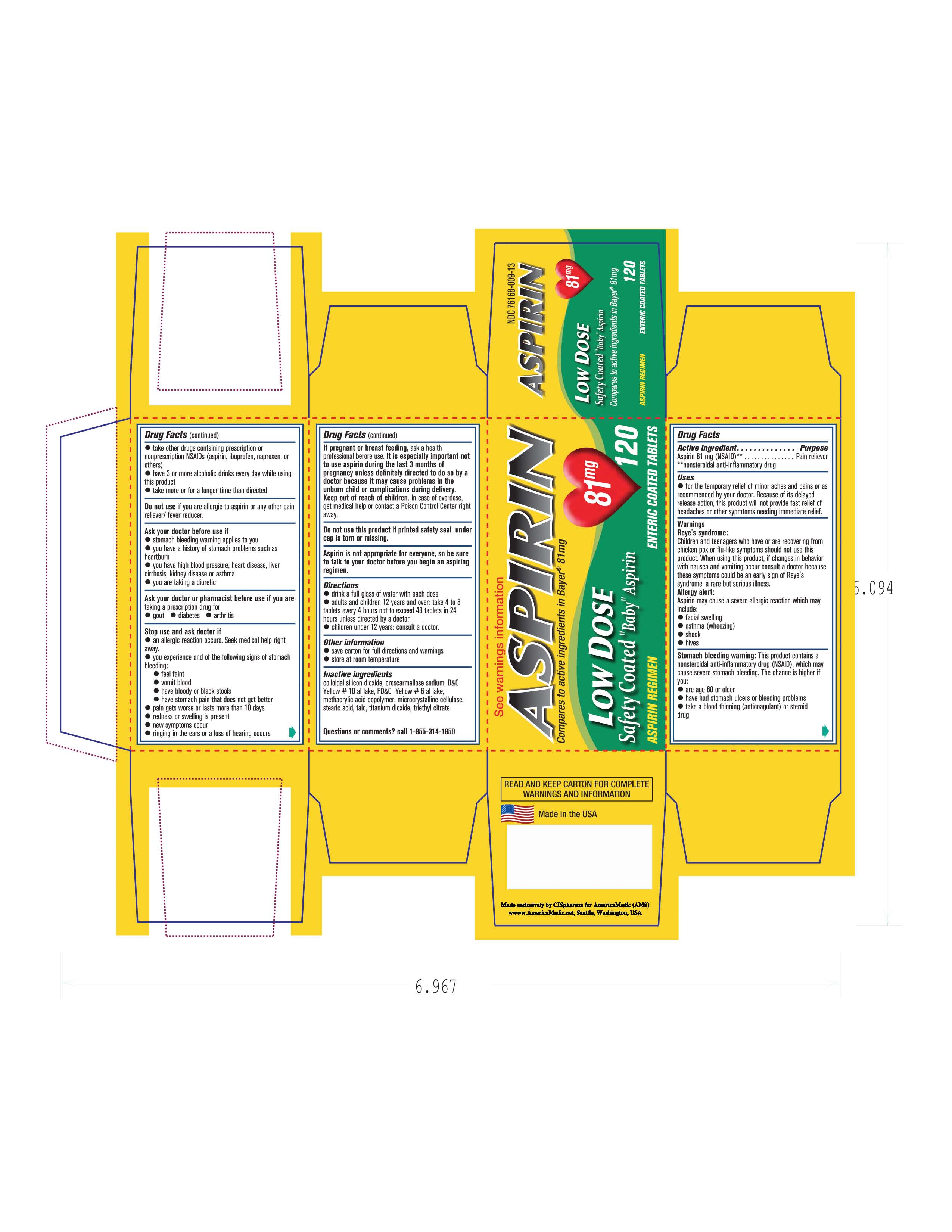 DRUG LABEL: Aspirin
NDC: 49638-001 | Form: TABLET
Manufacturer: America Medic
Category: otc | Type: HUMAN OTC DRUG LABEL
Date: 20120516

ACTIVE INGREDIENTS: ASPIRIN 81 mg/1 1
INACTIVE INGREDIENTS: D&C YELLOW NO. 10; FD&C YELLOW NO. 6; METHACRYLIC ACID - METHYL METHACRYLATE COPOLYMER (1:1); CELLULOSE, MICROCRYSTALLINE; STEARIC ACID; TITANIUM DIOXIDE; TRIETHYL CITRATE

Drug facts

ACTIVE INGREDIENT

Aspirin

PURPOSE

Internal Analgesic.

Keep out of reach of children. In case of overdose get medical help or contact a poison control center right away.

INDICATIONS AND USAGE

Oral Analgesic. Aspirin is not appropriate for everyone, so be sure to talk to a doctor before starting an Aspirin regimen.

Do not use this product if you are allergic to Aspirin or any other pain/fever product.
If pregnant or breastfeeding contact a doctor before using.
Contact a doctor or pharmacist if you are taking a prescription drug for-Gout, Diabetes or Arthritis.
Contact a doctor right away if: An allergic reaction occurs.

DOSAGE AND ADMINISTRATION

Drink a full glass of water with each dose.
Adults and children 12 years of age and up:Take 4-8 tablets every 4 hours not to exceed 48 tablets in 24hours unless indicated by a doctor.. Children under 12 years of age : Consult a Doctor.

INACTIVE INGREDIENT

Yellow # 10

Yellow # 6

Methacrylic Acid Copolymer

Microcrystalline Cellose

Stearic Acid

Titanium Dioxide

Triethyl Citrate

PACKAGE LABEL

Image of carton